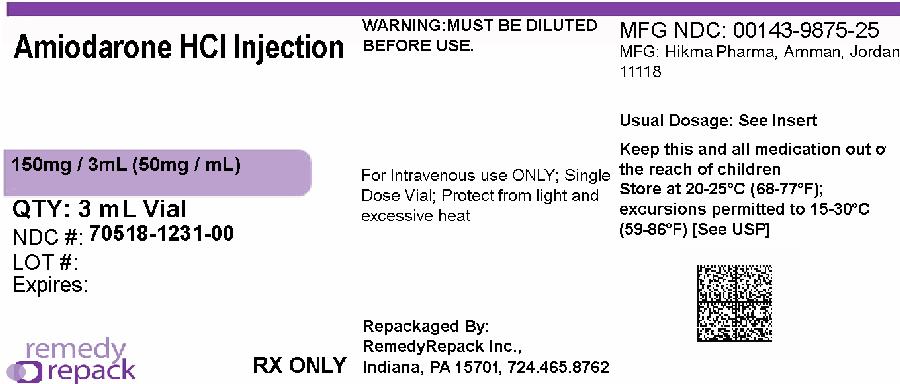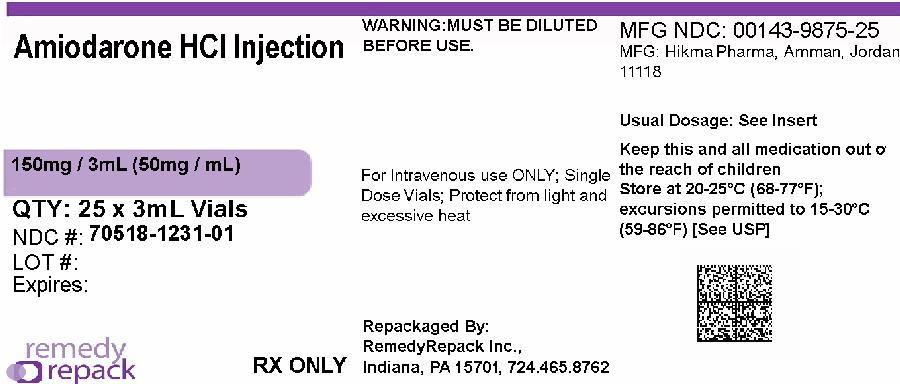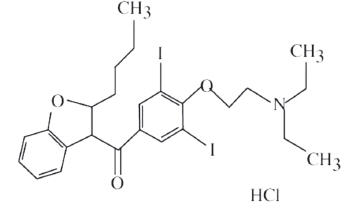 DRUG LABEL: Amiodarone Hydrochloride
NDC: 70518-1231 | Form: INJECTION, SOLUTION
Manufacturer: REMEDYREPACK INC.
Category: prescription | Type: HUMAN PRESCRIPTION DRUG LABEL
Date: 20260119

ACTIVE INGREDIENTS: AMIODARONE HYDROCHLORIDE 50 mg/1 mL
INACTIVE INGREDIENTS: POLYSORBATE 80 100 mg/1 mL; BENZYL ALCOHOL 20.2 mg/1 mL; WATER

HIGHLIGHTS OF PRESCRIBING INFORMATION

These highlights do not include all the information needed to use Amiodarone Hydrochloride Injection, USP safely and effectively. See full prescribing information for Amiodarone Hydrochloride Injection, USP.
AMIODARONE Hydrochloride Injection, USP for intravenous use
Initial U.S. Approval: 1995

1 INDICATIONS AND USAGE

Amiodarone Hydrochloride Injection, USP is an antiarrhythmic agent indicated for initiation of treatment and prophylaxis of frequently recurring ventricular fibrillation (VF) and hemodynamically unstable ventricular tachycardia (VT) in patients refractory to other therapy. (1)

2 DOSAGE AND ADMINISTRATION

- The recommended starting dose is about 1000 mg over the first 24 hours of therapy, delivered by the following infusion regimen (2):
  - -Initial Load: 150 mg per 100 mL (in D5W) infused over 10 minutes
  - -Followed by: 1 mg/min for 6 hours
  - -Followed by: 0.5 mg/min thereafter
- In the event of breakthrough episodes of VF or hemodynamically unstable VT (2):
  - -Repeat the Initial Load described above as needed (infused over 10 minutes)
- Increase the rate of the maintenance infusion to achieve effective arrhythmia suppression. (2)

3 DOSAGE FORMS AND STRENGTHS

Injection, 50 mg/mL (3)

4 CONTRAINDICATIONS

Amiodarone is contraindicated in patients with (4):

- Known hypersensitivity to any of the components of amiodarone, including iodine
- Cardiogenic shock
- Marked sinus bradycardia
- Second- or third-degree atrio-ventricular (AV) block unless a functioning pacemaker is available.

5 WARNINGS AND PRECAUTIONS

- Hypotension: Treat initially by slowing the infusion; additional standard therapy may be needed, including the following: vasopressor drugs, positive inotropic agents, and volume expansion. (5.1)
- Bradycardia and AV block: Treat by slowing the infusion rate or discontinuing amiodarone. (5.2)

6 ADVERSE REACTIONS

- The most common adverse reactions (1-2%) leading to discontinuation of intravenous amiodarone therapy are hypotension, asystole/cardiac arrest/pulseless electrical activity, VT, and cardiogenic shock. (6)
- Other important adverse reactions are, torsade de pointes (TdP), congestive heart failure, and liver function test abnormalities. (6)

To report SUSPECTED ADVERSE REACTIONS, contact Hikma Pharmaceuticals USA Inc. at 1-877-233-2001, or FDA at 1-800-FDA-1088 or www.fda.gov/medwatch.

7 DRUG INTERACTIONS

- Since amiodarone is a substrate for CYP3A and CYP2C8, drugs/substances that inhibit these isoenzymes may decrease the metabolism and increase serum concentration of amiodarone.
- Amiodarone inhibits p-glycoprotein and certain CYP450 enzymes, including CYP1A2, CYP2C9, CYP2D6, and CYP3A. This inhibition can result in unexpectedly high plasma levels of other drugs that are metabolized by those CYP450 enzymes or are substrates for p-glycoprotein.
- Fluoroquinolones, macrolide antibiotics, and azoles are known to cause QTc prolongation. There have been reports of QTc prolongation, with or without TdP, in patients taking amiodarone when fluoroquinolones, macrolide antibiotics, or azoles were administered concomitantly. (7)

8 USE IN SPECIFIC POPULATIONS

- Pregnancy: Use amiodarone during pregnancy only if the potential benefit to the mother justifies the risk to the fetus (8.1).
- Nursing mothers: Amiodarone and one of its major metabolites, desethylamiodarone (DEA), are excreted in human milk, suggesting that breastfeeding could expose the nursing infant to a significant dose of the drug. Advise mothers to discontinue breastfeeding (8.3).
- Pediatric use: The safety and efficacy of amiodarone in the pediatric population have not been established (8.4).

FULL PRESCRIBING INFORMATION

1 INDICATIONS AND USAGE

Amiodarone Hydrochloride Injection, USP is indicated for initiation of treatment and prophylaxis of frequently recurring ventricular fibrillation (VF) and hemodynamically unstable ventricular tachycardia (VT) in patients refractory to other therapy. Amiodarone Hydrochloride Injection, USP also can be used to treat patients with VT/VF for whom oral amiodarone is indicated, but who are unable to take oral medication. During or after treatment with Amiodarone Hydrochloride Injection, USP patients may be transferred to oral amiodarone therapy [see Dosage and Administration (2)] .

Use Amiodarone Hydrochloride Injection, USP for acute treatment until the patient's ventricular arrhythmias are stabilized. Most patients will require this therapy for 48 to 96 hours, but Amiodarone Hydrochloride Injection may be safely administered for longer periods if necessary.

2 DOSAGE AND ADMINISTRATION

Amiodarone shows considerable interindividual variation in response. Although a starting dose adequate to suppress life-threatening arrhythmias is needed, close monitoring with adjustment of dose is essential. The recommended starting dose of amiodarone is about 1000 mg over the first 24 hours of therapy, delivered by the following infusion regimen:

Table 1: AMIODARONE DOSE RECOMMENDATIONS: FIRST 24 HOURS
Loading infusions | FirstRapid: | 150 mg over the FIRST 10 minutes (15 mg/min). Add 3 mL of amiodarone (150 mg) to 100 mL D5W (concentration = 1.5 mg/mL). Infuse 100 mL over 10 minutes.
 | Followed bySlow: | 360 mg over the NEXT 6 hours (1 mg/min). Add 18 mL of amiodarone (900 mg) to 500 mL D5W (concentration = 1.8 mg/mL)
Maintenance infusion |  | 540 mg over the REMAINING 18 hours (0.5 mg/min). Decrease the rate of the slow loading infusion to 0.5 mg/min.

After the first 24 hours, continue the maintenance infusion rate of 0.5 mg/min (720 mg per 24 hours) utilizing a concentration of 1 to 6 mg/mL (Use a central venous catheter for amiodarone concentrations greater than 2 mg/mL). The rate of the maintenance infusion may be increased to achieve effective arrhythmia suppression.

In the event of breakthrough episodes of VF or hemodynamically unstable VT, use 150 mg supplemental infusions of amiodarone (mixed in 100 mL of D5W and infused over 10 minutes to minimize the potential for hypotension).

The first 24-hour dose may be individualized for each patient; however, in controlled clinical trials, mean daily doses above 2100 mg were associated with an increased risk of hypotension. Do not exceed an initial infusion rate of 30 mg/min.

Based on the experience from clinical studies of intravenous amiodarone, a maintenance infusion of up to 0.5 mg/min can be continued for 2 to 3 weeks regardless of the patient's age, renal function, or left ventricular function. There has been limited experience in patients receiving intravenous amiodarone for longer than 3 weeks.

The surface properties of solutions containing injectable amiodarone are altered such that the drop size may be reduced. This reduction may lead to underdosage of the patient by up to 30% if drop counter infusion sets are used. Amiodarone must be delivered by a volumetric infusion pump.

Administer amiodarone, whenever possible, through a central venous catheter dedicated to that purpose. Use an in-line filter during administration.

Intravenous amiodarone loading infusions at much higher concentrations and rates of infusion much faster than recommended have resulted in hepatocellular necrosis and acute renal failure, leading to death [see Warnings and Precautions (5.3)] .

Intravenous amiodarone concentrations greater than 3 mg/mL in D5W have been associated with a high incidence of peripheral vein phlebitis; however, concentrations of 2.5 mg/mL or less appear to be less irritating. Therefore, for infusions longer than 1 hour, do not exceed amiodarone concentrations of 2 mg/mL, unless a central venous catheter is used [see Adverse Reactions (6.2)] .

Amiodarone infusions exceeding 2 hours must be administered in glass or polyolefin bottles containing D5W. Do not use evacuated glass containers for admixing, as incompatibility with a buffer in the container may cause precipitation.

Amiodarone adsorbs to polyvinyl chloride (PVC) tubing, but all of the clinical experience has been with PVC tubing and the concentrations and rates of infusion provided in DOSAGE AND ADMINISTRATION reflect dosing in these studies.

Amiodarone has been found to leach out plasticizers, including DEHP [di-(2-ethylhexyl)phthalate] from intravenous tubing (including PVC tubing). The degree of leaching increases when infusing amiodarone at higher concentrations and lower flow rates than provided in DOSAGE AND ADMINISTRATION. Polysorbate 80, a component of amiodarone injection, is also known to leach DEHP from PVC [see Description (11)] .

Amiodarone does not need to be protected from light during administration.

NOTE: Inspect parenteral drug products for particulate matter and discoloration prior to administration, whenever solution and container permit.

Table 2: AMIODARONE HYDROCHLORIDE SOLUTION STABILITY
Solution | Concentration (mg/mL) | Container | Comments
5% Dextrose in Water (D5W) | 1 to 6 | PVC | Physically compatible, with amiodarone loss <10% at 2 hours at room temperature.
5% Dextrose in Water (D5W) | 1 to 6 | Polyolefin, Glass | Physically compatible, with no amiodarone loss at 24 hours at room temperature.

Admixture Incompatibility

Amiodarone in D5W is incompatible with the drugs shown in Table 3.

Table 3: Y-SITE INJECTION INCOMPATIBILITY
Drug | Vehicle | Amiodarone Concentration | Comments
Aminophylline | D5W | 4 mg/mL | Precipitate
Cefamandole Nafate | D5W | 4 mg/mL | Precipitate
Cefazolin Sodium | D5W | 4 mg/mL | Precipitate
Mezlocillin Sodium | D5W | 4 mg/mL | Precipitate
Heparin Sodium | D5W | -- | Precipitate
Sodium Bicarbonate | D5W | 3 mg/mL | Precipitate

Intravenous to Oral Transition

Patients whose arrhythmias have been suppressed by amiodarone may be switched to oral amiodarone. When changing to oral amiodarone therapy, clinical monitoring is recommended, particularly for elderly patients. See package insert for oral amiodarone.

Since grapefruit juice is known to inhibit CYP3A-mediated metabolism of oral amiodarone in the intestinal mucosa, resulting in increased plasma levels of amiodarone, do not drink grapefruit juice during treatment with oral amiodarone [see Drug Interactions (7)] .

Table 4 provides suggested doses of oral amiodarone to be initiated after varying durations of amiodarone administration. These recommendations are made on the basis of a similar total body amount of amiodarone delivered by the intravenous and oral routes, based on 50% bioavailability of oral amiodarone.

Table 4: RECOMMENDATIONS FOR ORAL DOSAGE AFTER INTRAVENOUS INFUSION
Duration of Amiodarone Infusion [Assuming a 720 mg/day infusion (0.5 mg/min).] | Initial Daily Dose of Oral Amiodarone
< 1 week | 800 to 1600 mg
1-3 weeks | 600 to 800 mg
> 3 weeks [Intravenous amiodarone is not intended for maintenance treatment.] | 400 mg

3 DOSAGE FORMS AND STRENGTHS

Injection, 50 mg/mL

4 CONTRAINDICATIONS

Amiodarone is contraindicated in patients with:

- Known hypersensitivity to any of the components of amiodarone, including iodine. Hypersensitivity reactions may involve rash, angioedema, cutaneous/mucosal hemorrhage (bleeding), fever, arthralgias (joint pains), eosinophilia (abnormal blood counts), urticaria (hives), thrombotic thrombocytopenic purpura, or severe periarteritis (inflammation around blood vessels).
- Cardiogenic shock.
- Marked sinus bradycardia.
- Second- or third-degree atrio-ventricular (AV) block unless a functioning pacemaker is available.

5 WARNINGS AND PRECAUTIONS

Amiodarone should be administered only by physicians who are experienced in the treatment of life-threatening arrhythmias, who are thoroughly familiar with the risks and benefits of amiodarone therapy, and who have access to facilities adequate for monitoring the effectiveness and side effects of treatment.

5.1 Hypotension

Hypotension is the most common adverse reaction seen with intravenous amiodarone. In clinical trials, treatment-emergent, drug-related hypotension was reported as an adverse effect in 288 (16%) of 1836 patients treated with intravenous amiodarone. Clinically significant hypotension during infusions was seen most often in the first several hours of treatment and was not dose related, but appeared to be related to the rate of infusion. Hypotension necessitating alterations in intravenous amiodarone therapy was reported in 3% of patients, with permanent discontinuation required in less than 2% of patients.

Treat hypotension initially by slowing the infusion; additional standard therapy may be needed, including the following: vasopressor drugs, positive inotropic agents, and volume expansion. Monitor the initial rate of infusion closely and do not exceed the recommended rate [see Dosage and Administration (2)] .

In some cases, hypotension may be refractory and result in a fatal outcome [see Adverse Reactions (6.2)] .

5.2 Bradycardia and Atrio-ventricular Block

In 90 (4.9%) of 1836 patients in clinical trials, drug-related bradycardia that was not dose-related occurred while they were receiving intravenous amiodarone for life-threatening VT/VF. Treat bradycardia by slowing the infusion rate or discontinuing amiodarone. In some patients, a pacemaker is required. Despite such measures, bradycardia was progressive and terminal in 1 patient during the controlled trials. Treat patients with a known predisposition to bradycardia or AV block with amiodarone in a setting where a temporary pacemaker is available.

5.3 Liver Enzyme Elevations

Elevations of blood hepatic enzyme values [alanine aminotransferase (ALT), aspartate aminotransferase (AST), and gamma-glutamyl transferase (GGT)] are commonly seen in patients with immediately life-threatening VT/VF. Interpreting elevated AST activity can be difficult because the values may be elevated in patients who have had recent myocardial infarction, congestive heart failure, or multiple electrical defibrillations. Approximately 54% of patients receiving intravenous amiodarone in clinical studies had baseline liver enzyme elevations, and 13% had clinically significant elevations. In 81% of patients with both baseline and on-therapy data available, the liver enzyme elevations either improved during therapy or remained at baseline levels. Baseline abnormalities in hepatic enzymes are not a contraindication to treatment.

Acute, centrolobular confluent hepatocellular necrosis leading to hepatic coma, acute renal failure, and death has been associated with the administration of intravenous amiodarone at a much higher loading dose concentration and much faster rate of infusion than recommended (see Dosage and Administration (2)) .

In patients with life-threatening arrhythmias, the potential risk of hepatic injury should be weighed against the potential benefit of amiodarone therapy. Carefully monitor patients receiving amiodarone for evidence of progressive hepatic injury. In such cases, consider reducing the rate of administration or withdrawing amiodarone.

5.4 Proarrhythmia

Amiodarone may cause a worsening of existing arrhythmias or precipitate a new arrhythmia. Proarrhythmia, primarily torsade de pointes (TdP), has been associated with prolongation, by intravenous amiodarone, of the QTc interval to 500 ms or greater. Although QTc prolongation occurred frequently in patients receiving intravenous amiodarone, TdP or new-onset VF occurred infrequently (less than 2%). Monitor patients for QTc prolongation during infusion with amiodarone. Reserve the combination of amiodarone with other antiarrhythmic therapies that prolong the QTc to patients with life-threatening ventricular arrhythmias who are incompletely responsive to a single agent.

Fluoroquinolones, macrolide antibiotics, and azoles are known to cause QTc prolongation. There have been reports of QTc prolongation, with or without TdP, in patients taking amiodarone when fluoroquinolones, macrolide antibiotics, or azoles were administered concomitantly [see Drug Interactions (7)] .

Amiodarone causes thyroid dysfunction in some patients, which may lead to potentially fatal breakthrough or exacerbated arrhythmias.

5.5 Pulmonary Disorders

Early-onset Pulmonary Toxicity

There have been postmarketing reports of acute-onset (days to weeks) pulmonary injury in patients treated with intravenous amiodarone. Findings have included pulmonary infiltrates and masses on X-ray, bronchospasm, wheezing, fever, dyspnea, cough, hemoptysis, and hypoxia. Some cases have progressed to respiratory failure or death.

ARDS

Two percent (2%) of patients were reported to have adult respiratory distress syndrome (ARDS) during clinical studies involving 48 hours of therapy.

Pulmonary Fibrosis

Only 1 of more than 1000 patients treated with intravenous amiodarone in clinical studies developed pulmonary fibrosis. In that patient, the condition was diagnosed 3 months after treatment with intravenous amiodarone, during which time the patient received oral amiodarone. Pulmonary toxicity is a well-recognized complication of long-term amiodarone use (see package insert for oral amiodarone).

5.6 Loss of Vision

Cases of optic neuropathy and optic neuritis, usually resulting in visual impairment, have been reported in patients treated with oral amiodarone. In some cases, visual impairment has progressed to permanent blindness. Optic neuropathy and neuritis may occur at any time following initiation of therapy. A causal relationship to the drug has not been clearly established. Perform an ophthalmic examination if symptoms of visual impairment appear, such as changes in visual acuity and decreases in peripheral vision. Re-evaluate the necessity of amiodarone therapy if optic neuropathy or neuritis is suspected. Perform regular ophthalmic examination, including fundoscopy and slit-lamp examination, during administration of amiodarone.

5.7 Long-Term Use

There has been limited experience in patients receiving intravenous amiodarone for longer than 3 weeks. See package insert for oral amiodarone.

5.8 Thyroid Abnormalities

Amiodarone inhibits peripheral conversion of thyroxine (T4) to triiodothyronine (T3) and may cause increased T4 levels, decreased T3 levels, and increased levels of inactive reverse T3 (rT3) in clinically euthyroid patients. Amiodarone is also a potential source of large amounts of inorganic iodine and can cause either hypothyroidism or hyperthyroidism. Evaluate thyroid function prior to treatment and periodically thereafter, particularly in elderly patients, and in any patient with a history of thyroid nodules, goiter, or other thyroid dysfunction. Because of the slow elimination of amiodarone and its metabolites, high plasma iodide levels, altered thyroid function, and abnormal thyroid-function tests may persist for months following amiodarone withdrawal.

There have been postmarketing reports of thyroid nodules/thyroid cancer in patients treated with amiodarone. In some instances hyperthyroidism was also present [see Adverse Reactions (6.2)] .

Hyperthyroidism and Thyrotoxicosis

Hyperthyroidism occurs in about 2% of patients receiving amiodarone, but the incidence may be higher among patients with prior inadequate dietary iodine intake. Amiodarone-induced hyperthyroidism usually poses a greater hazard to the patient than hypothyroidism because of the possibility of thyrotoxicosis and arrhythmia breakthrough or aggravation, all of which may result in death. There have been reports of death associated with amiodarone-induced thyrotoxicosis. Consider the possibility of hyperthyroidism if any new signs of arrhythmia appear.

Identify hyperthyroidism by relevant clinical signs and symptoms, subnormal serum levels of thyroid stimulating hormone (TSH), abnormally elevated serum free T4, and elevated or normal serum T3. Since arrhythmia breakthroughs may accompany amiodarone-induced hyperthyroidism, aggressive medical treatment is indicated, including, if possible, dose reduction or withdrawal of amiodarone. Amiodarone hyperthyroidism may be followed by a transient period of hypothyroidism.

The institution of antithyroid drugs, β-adrenergic blockers or temporary corticosteroid therapy may be necessary. The action of antithyroid drugs may be especially delayed in amiodarone-induced thyrotoxicosis because of substantial quantities of preformed thyroid hormones stored in the gland. Radioactive iodine therapy is contraindicated because of the low radioiodine uptake associated with amiodarone-induced hyperthyroidism.

When aggressive treatment of amiodarone-induced thyrotoxicosis has failed or amiodarone cannot be discontinued because it is the only drug effective against the resistant arrhythmia, surgical management may be an option. Experience with thyroidectomy as a treatment for amiodarone-induced thyrotoxicosis is limited, and this form of therapy could induce thyroid storm. Therefore, surgical and anesthetic management require careful planning.

Neonatal Hypo- or Hyperthyroidism

Amiodarone can cause fetal harm when administered to a pregnant woman. Although amiodarone use during pregnancy is uncommon, there have been a small number of published reports of congenital goiter/hypothyroidism and hyperthyroidism associated with oral administration. Inform the patient of the potential hazard to the fetus if amiodarone is administered during pregnancy or if the patient becomes pregnant while taking amiodarone.

Hypothyroidism

Hypothyroidism has been reported in 2 to 4% of patients in most series, but in 8 to 10% in some series. This condition may be identified by relevant clinical symptoms and particularly by elevated serum TSH levels. In some clinically hypothyroid amiodarone-treated patients, free thyroxine index values may be normal. Manage hypothyroidism by reducing the amiodarone dose and considering the need for thyroid hormone supplement. However, therapy must be individualized, and it may be necessary to discontinue amiodarone in some patients.

5.9 Surgery

Perform close perioperative monitoring in patients undergoing general anesthesia who are on amiodarone therapy as they may be more sensitive to the myocardial depressant and conduction defects of halogenated inhalational anesthetics.

5.10 Corneal Refractive Laser Surgery

Advise patients that most manufacturers of corneal refractive laser surgery devices contraindicate corneal refractive laser surgery in patients taking amiodarone.

5.11 Electrolyte Disturbances

Correct hypokalemia or hypomagnesemia whenever possible before initiating treatment with amiodarone, as these disorders can exaggerate the degree of QTc prolongation and increase the potential for TdP. Give special attention to electrolyte and acid-base balance in patients experiencing severe or prolonged diarrhea or in patients receiving concomitant diuretics.

6 ADVERSE REACTIONS

6.1 Clinical Trials Experience

Because clinical trials are conducted under widely varying conditions, adverse reaction rates observed in the clinical trials of a drug cannot be directly compared to rates in the clinical trials of another drug and may not reflect the rates observed in practice.

In a total of 1836 patients in controlled and uncontrolled clinical trials, 14% of patients received intravenous amiodarone for at least one week, 5% received it for at least 2 weeks, 2% received it for at least 3 weeks, and 1% received it for more than 3 weeks, without an increased incidence of severe adverse reactions. The mean duration of therapy in these studies was 5.6 days; median exposure was 3.7 days.

The most important adverse reactions were hypotension, asystole/cardiac arrest/pulseless electrical activity (PEA), cardiogenic shock, congestive heart failure, bradycardia, liver function test abnormalities, VT, and AV block. Overall, treatment was discontinued for about 9% of the patients because of adverse reactions. The most common adverse reactions leading to discontinuation of intravenous amiodarone therapy were hypotension (1.6%), asystole/cardiac arrest/PEA (1.2%), VT (1.1%), and cardiogenic shock (1%).

Table 5 lists the most common (incidence ≥2%) adverse reactions during intravenous amiodarone therapy considered at least possibly drug-related. These data were collected in clinical trials involving 1836 patients with life-threatening VT/VF. Data from all assigned treatment groups are pooled because none of the adverse reactions appeared to be dose-related.

Table 5: ADVERSE REACTIONS IN PATIENTS RECEIVING INTRAVENOUS AMIODARONE IN CONTROLLED AND OPEN-LABEL STUDIES (≥ 2% INCIDENCE)
Study Event | Controlled Studies (n = 814) | Open-Label Studies (n = 1022) | Total (n = 1836)
Body as a whole
Fever | 24 (2.9%) | 13 (1.2%) | 37 (2.0%)
Cardiovascular System
Bradycardia | 49 (6.0%) | 41 (4.0%) | 90 (4.9%)
Congestive heart failure | 18 (2.2%) | 21 (2.0%) | 39 (2.1%)
Heart arrest | 29 (3.5%) | 26 (2.5%) | 55 (2.9%)
Hypotension | 165 (20.2%) | 123 (12.0%) | 288 (15.6%)
Ventricular tachycardia | 15 (1.8%) | 30 (2.9%) | 45 (2.4%)
Digestive System
Liver function tests abnormal | 35 (4.2%) | 29 (2.8%) | 64 (3.4%)
Nausea | 29 (3.5%) | 43 (4.2%) | 72 (3.9%)

Other adverse reactions reported in less than 2% of patients receiving intravenous amiodarone in controlled and uncontrolled studies included the following: abnormal kidney function, atrial fibrillation, diarrhea, increased ALT, increased AST, lung edema, nodal arrhythmia, prolonged QT interval, respiratory disorder, shock, sinus bradycardia, Stevens-Johnson syndrome, thrombocytopenia, VF, and vomiting.

6.2 Postmarketing Experience

The following adverse reactions have been identified during post-approval use of amiodarone. Because these reactions are reported voluntarily from a population of uncertain size, it is not always possible to reliably estimate their frequency or establish a causal relationship to drug exposure.

Body as a Whole:anaphylactic/anaphylactoid reaction (including shock), fever

Cardiovascular:hypotension (sometimes fatal), sinus arrest

Dermatologic:toxic epidermal necrolysis (sometimes fatal), exfoliative dermatitis, erythema multiforme, Stevens-Johnson syndrome, skin cancer, pruritus, angioedema

Endocrine:syndrome of inappropriate antidiuretic hormone secretion (SIADH)

Hematologic:pancytopenia, neutropenia, hemolytic anemia, aplastic anemia, thrombocytopenia, agranulocytosis, granuloma

Hepatic:hepatitis, cholestatic hepatitis, cirrhosis

Injection Site Reactions:pain, erythema, edema, pigment changes, venous thombosis, phlebitis, thrombophlebitis, cellulitis, necrosis, and skin sloughing

Musculoskeletal:myopathy, muscle weakness, rhabdomyolysis

Nervous System:hallucination, confusional state, disorientation, and delirium, pseudotumor cerebri

Pancreatic:pancreatitis

Renal:renal impairment, renal insufficiency, acute renal failure

Respiratory:bronchospasm, possibly fatal respiratory disorders (including distress, failure, arrest and ARDS), bronchiolitis obliterans organizing pneumonia (possibly fatal), dyspnea, cough, hemoptysis, wheezing, hypoxia, pulmonary infiltrates, and /or mass, pleuritis

Thyroid:thyroid nodules/thyroid cancer

Vascular:vasculitis

7 DRUG INTERACTIONS

Amiodarone is metabolized to the active metabolite desethylamiodarone by the cytochrome P450 (CYP450) enzyme group, specifically cytochromes P4503A4 (CYP3A) and CYP2C8. The CYP3A isoenzyme is present in both the liver and intestines.

Amiodarone is an inhibitor of CYP3A. Therefore, amiodarone has the potential for interactions with drugs or substances that may be substrates, inhibitors or inducers of CYP3A. While only a limited number of in vivodrug-drug interactions with amiodarone have been reported, chiefly with the oral formulation, the potential for other interactions should be anticipated. This is especially important for drugs associated with serious toxicity, such as other antiarrhythmics. If such drugs are needed, reassess their dose and, where appropriate, measure plasma concentrations. In view of the long and variable half-life of amiodarone, potential for drug interactions exists not only with concomitant medication but also with drugs administered after discontinuation of amiodarone.

Since amiodarone is a substrate for CYP3A and CYP2C8, drugs/substances that inhibit these isoenzymes may decrease the metabolism and increase serum concentration of amiodarone. Reported examples include the following:

Protease inhibitors:
Protease inhibitors are known to inhibit CYP3A to varying degrees. A case report of one patient taking amiodarone 200 mg and indinavir 800 mg three times a day resulted in increases in amiodarone concentrations from 0.9 mg/L to 1.3 mg/L. DEA concentrations were not affected. There was no evidence of toxicity. Consider monitoring for amiodarone toxicity and serial measurement of amiodarone serum concentration during concomitant protease inhibitor therapy.

Histamine H1antagonists:
Loratadine, a non-sedating antihistaminic, is metabolized primarily by CYP3A. QT interval prolongation and TdP have been reported with the coadministration of loratadine and amiodarone.

Histamine H2antagonists:
Cimetidineinhibits CYP3A and can increase serum amiodarone levels.

Antidepressants:
Trazodone, an antidepressant, is metabolized primarily by CYP3A. QT interval prolongation and TdP have been reported with the coadministration of trazodone and amiodarone.

Other substances:
Grapefruit juicegiven to healthy volunteers increased amiodarone AUC by 50% and Cmaxby 84%, resulting in increased plasma levels of amiodarone. Do not take grapefruit juice during treatment with amiodarone.

Amiodarone inhibits p-glycoprotein and certain CYP450 enzymes, including CYP1A2, CYP2C9, CYP2D6, and CYP3A. This inhibition can result in unexpectedly high plasma levels of other drugs which are metabolized by those CYP450 enzymes or are substrates for p-glycoprotein. Reported examples of this interaction include the following:

Immunosuppressives:
Cyclosporine(CYP3A substrate) administered in combination with oral amiodarone has been reported to produce persistently elevated plasma concentrations of cyclosporine resulting in elevated creatinine, despite reduction in dose of cyclosporine.

HMG-CoA Reductase Inhibitors:
Simvastatin(CYP3A substrate) in combination with amiodarone has been associated with reports of myopathy/rhabdomyolysis.

Cardiovasculars:
Cardiac glycosides: In patients receiving digoxintherapy, administration of oral amiodarone regularly results in an increase in serum digoxin concentration that may reach toxic levels with resultant clinical toxicity. Amiodarone taken concomitantly with digoxin increases the serum digoxin concentration by 70% after one day. On administration of oral amiodarone, review the need for digitalis therapy and reduce the dose of digitalis by approximately 50% or discontinue digitalis. If digitalis treatment is continued, monitor serum levels closely and observe patients for clinical evidence of toxicity.

Antiarrhythmics:
Other antiarrhythmic drugs, such as quinidine, procainamide, disopyramide, and phenytoin,have been used concurrently with amiodarone. There have been case reports of increased steady-state levels of quinidine, procainamide, and phenytoin during concomitant therapy with amiodarone. Phenytoin decreases serum amiodarone levels. Amiodarone taken concomitantly with quinidine increases quinidine serum concentration by 33% after two days. Amiodarone taken concomitantly with procainamide for less than seven days increases plasma concentrations of procainamide and n-acetyl procainamide by 55% and 33%, respectively. Reduce quinidine and procainamide doses by one-third when either is administered with amiodarone.

Plasma levels of flecainidehave been reported to increase in the presence of oral amiodarone; adjust the dose of flecainide when these drugs are administered concomitantly. In general, initiate any added antiarrhythmic drug at a lower than usual dose and monitor the patient carefully.

Reserve the combination of amiodarone with other antiarrhythmic therapy to patients with life-threatening ventricular arrhythmias who are incompletely responsive to a single agent or incompletely responsive to amiodarone. During transfer to oral amiodarone, reduce the dose levels of previously administered agents by 30 to 50% several days after the addition of oral amiodarone. Review the continued need for the other antiarrhythmic agent after the effects of amiodarone have been established, and attempt discontinuation. If the treatment is continued, carefully monitor these patients for adverse effects, especially for conduction disturbances and exacerbation of tachyarrhythmias. In amiodarone-treated patients who require additional antiarrhythmic therapy, the initial dose of such agents should be approximately half of the usual recommended dose.

Antihypertensives:
Use amiodarone with caution in patients receiving ß-receptor blocking agents (e.g., propranolol, a CYP3A inhibitor) or calcium channel antagonists (e.g., verapamil, a CYP3A substrate, and diltiazem, a CYP3A inhibitor) because of the possible potentiation of bradycardia, sinus arrest, and AV block; if necessary, amiodarone can continue to be used after insertion of a pacemaker in patients with severe bradycardia or sinus arrest.

Anticoagulants:
Potentiation of warfarin-type (CYP2C9 and CYP3A substrate) anticoagulant response is almost always seen in patients receiving amiodarone and can result in serious or fatal bleeding. Since the concomitant administration of warfarin with amiodarone increases the prothrombin time by 100% after 3 to 4 days, reduce the dose of the anticoagulant by one-third to one-half, and monitor prothrombin times closely.

Clopidogrel, an inactive thienopyridine prodrug, is metabolized in the liver by CYP3A to an active metabolite. A potential interaction between clopidogrel and amiodarone resulting in ineffective inhibition of platelet aggregation has been reported.

Some drugs/substances are known to accelerate the metabolism of amiodarone by stimulating the synthesis of CYP3A (enzyme induction). This may lead to low amiodarone serum levels and potential decrease in efficacy. Reported examples of this interaction include the following:

Antibiotics:
Rifampinis a potent inducer of CYP3A. Administration of rifampin concomitantly with oral amiodarone has been shown to result in decreases in serum concentrations of amiodarone and desethylamiodarone.

Other substances, including herbal preparations:
St. John's Wort(Hypericum perforatum) induces CYP3A. Since amiodarone is a substrate for CYP3A, St. John's Wort likely reduces amiodarone levels.

Other reported interactions with amiodarone:
Fentanyl(CYP3A substrate) in combination with amiodarone may cause hypotension, bradycardia, and decreased cardiac output.

Sinus bradycardia has been reported with oral amiodarone in combination with lidocaine(CYP3A substrate) given for local anesthesia. Seizure, associated with increased lidocaine concentrations, has been reported with concomitant administration of intravenous amiodarone.

Dextromethorphanis a substrate for both CYP2D6 and CYP3A. Amiodarone inhibits CYP2D6.

Cholestyramineincreases enterohepatic elimination of amiodarone and may reduce its serum levels and t½.

Disopyramidecauses QT prolongation which could induce arrhythmia.

Fluoroquinolones, macrolide antibiotics, and azolesare known to cause QTc prolongation. There have been reports of QTc prolongation, with or without TdP, in patients taking amiodarone when fluoroquinolones, macrolide antibiotics, or azoles were administered concomitantly [see Warnings and Precautions (5.4)] .

Hemodynamic and electrophysiologic interactions have also been observed after concomitant administration with propranolol, diltiazem, and verapamil.

Volatile Anesthetic Agents: Patients who are on amiodarone therapy may be more sensitive to the myocardial depressant and conduction defects of halogenated inhalational anesthetics [see Warnings and Precautions (5.9)] .

In addition to the interactions noted above, chronic (> 2 weeks) oralamiodarone administration impairs metabolism of phenytoin, dextromethorphan, and methotrexate.

8 USE IN SPECIFIC POPULATIONS

8.1 Pregnancy

Pregnancy Category D [see Warnings and Precautions (5.8)] .

In addition to causing infrequent congenital goiter/hypothyroidism and hyperthyroidism, amiodarone has caused a variety of adverse effects in animals.

In a reproductive study in which amiodarone was given intravenously to rabbits at dosages of 5, 10, or 25 mg/kg per day (about 0.1, 0.3, and 0.7 times the maximum recommended human dose [MRHD] on a body surface area basis), maternal deaths occurred in all groups, including controls. Embryotoxicity (as manifested by fewer full-term fetuses and increased resorptions with concomitantly lower litter weights) occurred at dosages of 10 mg/kg and above. No evidence of embryotoxicity was observed at 5 mg/kg and no teratogenicity was observed at any dosages.

In a teratology study in which amiodarone was administered by continuous IV infusion to rats at dosages of 25, 50, or 100 mg/kg per day (about 0.4, 0.7, and 1.4 times the MRHD when compared on a body surface area basis), maternal toxicity (as evidenced by reduced weight gain and food consumption) and embryotoxicity (as evidenced by increased resorptions, decreased live litter size, reduced body weights, and retarded sternum and metacarpal ossification) were observed in the 100 mg/kg group.

Use amiodarone during pregnancy only if the potential benefit to the mother justifies the risk to the fetus.

8.2 Labor and Delivery

It is not known whether the use of amiodarone during labor or delivery has any immediate or delayed adverse effects. Preclinical studies in rodents have not shown any effect on the duration of gestation or on parturition.

8.3 Nursing Mothers

Amiodarone and one of its major metabolites, desethylamiodarone (DEA), are excreted in human milk, suggesting that breastfeeding could expose the nursing infant to a significant dose of the drug. Nursing offspring of lactating rats administered amiodarone have demonstrated reduced viability and reduced body weight gains. The risk of exposing the infant to amiodarone must be weighed against the potential benefit of arrhythmia suppression in the mother. Advise the mother to discontinue nursing.

8.4 Pediatric Use

The safety and effectiveness of amiodarone in pediatric patients have not been established; therefore, the use of amiodarone in pediatric patients is not recommended. In a pediatric trial of 61 patients, aged 30 days to 15 years, hypotension (36%), bradycardia (20%), and AV block (15%) were common dose-related adverse reactions and were severe or life-threatening in some cases. Injection site reactions were seen in 5 (25%) of the 20 patients receiving intravenous amiodarone through a peripheral vein irrespective of dose regimen.

Amiodarone injection contains the preservative benzyl alcohol [see Description (11)] . There have been reports of fatal "gasping syndrome" in neonates (children less than one month of age) following the administration of intravenous solutions containing the preservative benzyl alcohol. Symptoms include a striking onset of gasping respiration, hypotension, bradycardia, and cardiovascular collapse.

8.5 Geriatric Use

Clinical studies of amiodarone did not include sufficient numbers of subjects aged 65 and over to determine whether they respond differently from younger subjects. Other reported clinical experience has not identified differences in responses between the elderly and younger patients. Carefully consider dose selection in an elderly patient. In general, start at the low end of the dosing range in the elderly to reflect the greater frequency of decreased hepatic, renal, or cardiac function, and concomitant disease or other drug therapy.

10 OVERDOSAGE

There have been cases, some fatal, of amiodarone overdose. Effects of an inadvertent overdose of intravenous amiodarone include hypotension, cardiogenic shock, bradycardia, AV block, and hepatotoxicity. Treat hypotension and cardiogenic shock by slowing the infusion rate or with standard therapy: vasopressor drugs, positive inotropic agents, and volume expansion. Bradycardia and AV block may require temporary pacing. Monitor hepatic enzyme concentrations closely. Amiodarone is not dialyzable.

11 DESCRIPTION

Amiodarone Hydrochloride Injection contains Amiodarone Hydrochloride (C25H29I2NO3•HCl), a class III antiarrhythmic drug. Amiodarone Hydrochloride is (2-butyl-3-benzo-furanyl)[4-[2-(diethylamino)ethoxy]-3,5-diiodophenyl]methanone hydrochloride.

Amiodarone Hydrochloride has the following structural formula:

Amiodarone Hydrochloride is a white to slightly yellow crystalline powder, and is very slightly soluble in water. It has a molecular weight of 681.78 and contains 37.3% iodine by weight. Amiodarone Hydrochloride Injection is a sterile clear, pale-yellow micellar solution visually free from particulates. Each milliliter of the amiodarone formulation contains 50 mg of amiodarone hydrochloride, 20.2 mg of benzyl alcohol, 100 mg of polysorbate 80, and water for injection.

Amiodarone Hydrochloride Injection contains polysorbate 80, which is known to leach di-(2-ethylhexyl)phthalate (DEHP) from polyvinylchloride (PVC) [(see Dosage and Administration (2)] .

12 CLINICAL PHARMACOLOGY

12.1 Mechanism of Action

Amiodarone is generally considered a class III antiarrhythmic drug, but it possesses electrophysiologic characteristics of all four Vaughan Williams classes. Like class I drugs, amiodarone blocks sodium channels at rapid pacing frequencies, and like class II drugs, amiodarone exerts a noncompetitive antisympathetic action. One of its main effects, with prolonged administration, is to lengthen the cardiac action potential, a class III effect. The negative chronotropic effect of amiodarone in nodal tissues is similar to the effect of class IV drugs. In addition to blocking sodium channels, amiodarone blocks myocardial potassium channels, which contributes to slowing of conduction and prolongation of refractoriness. The antisympathetic action and the block of calcium and potassium channels are responsible for the negative dromotropic effects on the sinus node and for the slowing of conduction and prolongation of refractoriness in the atrioventricular (AV) node. Its vasodilatory action can decrease cardiac workload and consequently myocardial oxygen consumption.

Intravenous amiodarone administration prolongs intranodal conduction (Atrial-His, AH) and refractoriness of the atrioventricular node (ERP AVN), but has little or no effect on sinus cycle length (SCL), refractoriness of the right atrium and right ventricle (ERP RA and ERP RV), repolarization (QTc), intraventricular conduction (QRS), and infra-nodal conduction (His-ventricular, HV). A comparison of the electrophysiologic effects of intravenous amiodarone and oral amiodarone is shown in the table below.

Table 6: EFFECTS OF INTRAVENOUS AND ORAL AMIODARONE ON ELECTROPHYSIOLOGIC PARAMETERS
Formulation | SCL | QRS | QTc | AH | HV | ERP RA | ERP RV | ERP AVN
Intravenous | ↔ | ↔ | ↔ | ↑ | ↔ | ↔ | ↔ | ↑
Oral | ↑ | ↔ | ↑ | ↑ | ↔ | ↑ | ↑ | ↑
↔ No change

At higher doses (>10 mg/kg) of intravenous amiodarone, prolongation of the ERP RV and modest prolongation of the QRS have been seen. These differences between oral and IV administration suggest that the initial acute effects of intravenous amiodarone may be predominately focused on the AV node, causing an intranodal conduction delay and increased nodal refractoriness due to slow channel blockade (class IV activity) and noncompetitive adrenergic antagonism (class II activity).

12.2 Pharmacodynamics

Intravenous amiodarone has been reported to produce negative inotropic and vasodilatory effects in animals and humans. In clinical studies of patients with refractory VF or hemodynamically unstable VT, treatment-emergent, drug-related hypotension occurred in 288 of 1836 patients (16%) treated with intravenous amiodarone. No correlations were seen between the baseline ejection fraction and the occurrence of clinically significant hypotension during infusion of intravenous amiodarone.

No data are available on the activity of DEA in humans, but in animals, it has significant electrophysiologic and antiarrhythmic effects generally similar to amiodarone itself. DEA's precise role and contribution to the antiarrhythmic activity of oral amiodarone are not certain. The development of maximal ventricular class III effects after oral amiodarone administration in humans correlates more closely with DEA accumulation over time than with amiodarone accumulation. On the other hand, after intravenous amiodarone administration, there is evidence of activity well before significant concentrations of DEA are attained [see Clinical Trials(14)] .

12.3 Pharmacokinetics

Disposition:

Amiodarone exhibits complex disposition characteristics after intravenous administration. Peak serum concentrations after single 5 mg/kg 15-minute intravenous infusions in healthy subjects range between 5 and 41 mg/L. Peak concentrations after 10-minute infusions of 150 mg intravenous amiodarone in patients with ventricular fibrillation (VF) or hemodynamically unstable ventricular tachycardia (VT) range between 7 and 26 mg/L. Due to rapid distribution, serum concentrations decline to 10% of peak values within 30 to 45 minutes after the end of the infusion. In clinical trials, after 48 hours of continued infusions (125, 500 or 1000 mg/day) plus supplemental (150 mg) infusions (for recurrent arrhythmias), amiodarone mean serum concentrations between 0.7 to 1.4 mg/L were observed (n=260).

Metabolism:

N-desethylamiodarone (DEA) is the major active metabolite of amiodarone in humans. DEA serum concentrations above 0.05 mg/L are not usually seen until after several days of continuous infusion but with prolonged therapy reach approximately the same concentration as amiodarone. Amiodarone is metabolized to DEA by the cytochrome P450 enzyme group, specifically cytochromes CYP3A and CYP2C8. The CYP3A isoenzyme is present in both the liver and intestines. The highly variable systemic availability of oral amiodarone may be attributed to large interindividual variability in CYP3A activity.

Distribution/Elimination:

From in vitrostudies, the protein binding of amiodarone is >96%. Amiodarone and DEA cross the placenta and both appear in breast milk. Neither amiodarone nor DEA is dialyzable.

Amiodarone is eliminated primarily by hepatic metabolism and biliary excretion and there is negligible excretion of amiodarone or DEA in urine. In studies in healthy subjects following single intravenous administration (5 mg/kg of amiodarone over 15 min), the plasma concentration vs. time profile could be characterized by linear sum of four exponential terms with terminal elimination half-lives (t½) of 9 - 36 days for amiodarone and 9 - 30 days for DEA. The clearance of amiodarone and DEA ranged between 63 - 231 mL/hr/kg and 140 - 400 mL/hr/kg, respectively. In clinical studies of 2 to 7 days, clearance of amiodarone after intravenous administration in patients with VT and VF ranged between 220 and 440 mL/hr/kg.

Special Populations:

Effect of Age:The pharmacokinetics of amiodarone and DEA are affected by age. Normal subjects over 65 years of age show lower clearances (about 100 mL/hr/kg) than younger subjects (about 150 mL/hr/kg) and an increase in t½from about 20 to 47 days.

Effect of Gender:Pharmacokinetics of amiodarone and DEA are similar in males and females.

Renal Impairment:Renal disease does not influence the pharmacokinetics of amiodarone or DEA.

Hepatic Impairment:After a single dose of intravenous amiodarone to cirrhotic patients, significantly lower Cmaxand average concentration values are seen for DEA, but mean amiodarone levels are unchanged.

Cardiac Disease:In patients with severe left ventricular dysfunction, the pharmacokinetics of amiodarone are not significantly altered but the terminal elimination t½of DEA is prolonged.

Although no dosage adjustment for patients with renal, hepatic, or cardiac abnormalities has been defined during chronic treatment with oral amiodarone, close clinical monitoring is prudent for elderly patients and those with severe left ventricular dysfunction.

Exposure-Response:

There is no established relationship between drug concentration and therapeutic response for short-term intravenous use.

13 NONCLINICAL TOXICOLOGY

13.1 Carcinogenesis, Mutagenesis, Impairment of Fertility

No carcinogenicity studies were conducted with intravenous administration of amiodarone. However, oral amiodarone caused a statistically significant, dose-related increase in the incidence of thyroid tumors (follicular adenoma and carcinoma) in rats. The incidence of thyroid tumors in rats was greater than the incidence in controls even at the lowest dose level tested, i.e., 5 mg/kg/day (much less, on a body surface area basis, than the maximum recommended human maintenance dose of 600 mg/day).

Mutagenicity studies conducted with amiodarone hydrochloride (Ames, micronucleus, and lysogenic induction tests) were negative.

No fertility studies were conducted with intravenous administration of amiodarone. However, in a study in which amiodarone hydrochloride was orally administered to male and female rats, beginning 9 weeks prior to mating, reduced fertility was observed at a dose level of 90 mg/kg/day (approximately 1.4 times the maximum recommended human maintenance dose of 600 mg/day).

14 CLINICAL STUDIES

Apart from studies in patients with VT or VF, described below, there are two other studies of amiodarone showing an antiarrhythmic effect before significant levels of DEA could have accumulated. A placebo-controlled study of intravenous amiodarone (300 mg over 2 hours followed by 1200 mg/day) in post-coronary artery bypass graft patients with supraventricular and 2- to 3-consecutive-beat ventricular arrhythmias showed a reduction in arrhythmias from 12 hours on. A baseline-controlled study using a similar IV regimen in patients with recurrent, refractory VT/VF also showed rapid onset of antiarrhythmic activity; amiodarone therapy reduced episodes of VT by 85% compared to baseline.

The acute effectiveness of intravenous amiodarone in suppressing recurrent VF or hemodynamically unstable VT is supported by two randomized, parallel, dose-response studies of approximately 300 patients each. In these studies, patients with at least two episodes of VF or hemodynamically unstable VT in the preceding 24 hours were randomly assigned to receive doses of approximately 125 or 1000 mg over the first 24 hours, an 8-fold difference. In one study, a middle dose of approximately 500 mg was evaluated. The dose regimen consisted of an initial rapid loading infusion, followed by a slower 6-hour loading infusion, and then an 18-hour maintenance infusion. The maintenance infusion was continued up to hour 48. Additional 10-minute infusions of 150 mg intravenous amiodarone were given for "breakthrough" VT/VF more frequently to the 125 mg dose group, thereby considerably reducing the planned 8-fold differences in total dose to 1.8- and 2.6-fold, respectively, in the two studies.

The prospectively defined primary efficacy end point was the rate of VT/VF episodes per hour. For both studies, the median rate was 0.02 episodes per hour in patients receiving the high dose and 0.07 episodes per hour in patients receiving the low dose, or approximately 0.5 versus 1.7 episodes per day (p=0.07, 2-sided, in both studies). In one study, the time to first episode of VT/VF was significantly prolonged (approximately 10 hours in patients receiving the low dose and 14 hours in patients receiving the high dose). In both studies, significantly fewer supplemental infusions were given to patients in the high-dose group. At the end of double-blind therapy or after 48 hours, all patients were given open access to whatever treatment (including intravenous amiodarone) was deemed necessary. Mortality was not affected in these studies.

16 HOW SUPPLIED/ STORAGE AND HANDLING

Amiodarone Hydrochloride Injection, USP 50 mg/mL, is supplied as follows:

NDC: 70518-1231-00

NDC: 70518-1231-01

PACKAGING: 3 mL in 1 VIAL, TYPE 0

PACKAGING: 25 in 1 BOX

Store at 20º-25ºC (68º-77ºF) [See USP Controlled Room Temperature].

Protect from light and excessive heat.

Use carton to protect contents from light until time of use.

Repackaged and Distributed By:

Remedy Repack, Inc.

625 Kolter Dr. Suite #4 Indiana, PA 1-724-465-8762

17 PATIENT COUNSELING INFORMATION

Amiodarone has the potential to cause serious side effects that limit its use to life-threatening and hemodynamically unstable cardiac arrhythmias. Advise female patients to discontinue nursing while being treated with amiodarone, as breast-feeding could expose the nursing infant to a significant dose of the drug. Recommend that patients avoid grapefruit juice, over-the-counter cough medicine (which commonly contain dextromethorphan), and St. John's Wort. Inform patients that most manufacturers of corneal refractive laser surgery devices contraindicate corneal refractive laser surgery in patients taking amiodarone. Discuss the symptoms of hypo- and hyper-thyroidism, particularly if patients will be transitioned to oral amiodarone.

Repackaged By / Distributed By: RemedyRepack Inc.

625 Kolter Drive, Indiana, PA 15701

(724) 465-8762

PACKAGE LABEL

DRUG: Amiodarone Hydrochloride

GENERIC: Amiodarone Hydrochloride

DOSAGE: INJECTION, SOLUTION

ADMINSTRATION: INTRAVENOUS

NDC: 70518-1231-0

NDC: 70518-1231-1

PACKAGING: 3 mL in 1 VIAL

OUTER PACKAGING: 25 in 1 BOX

ACTIVE INGREDIENT(S):

- AMIODARONE HYDROCHLORIDE 50mg in 1mL

INACTIVE INGREDIENT(S):

- WATER
- POLYSORBATE 80
- BENZYL ALCOHOL